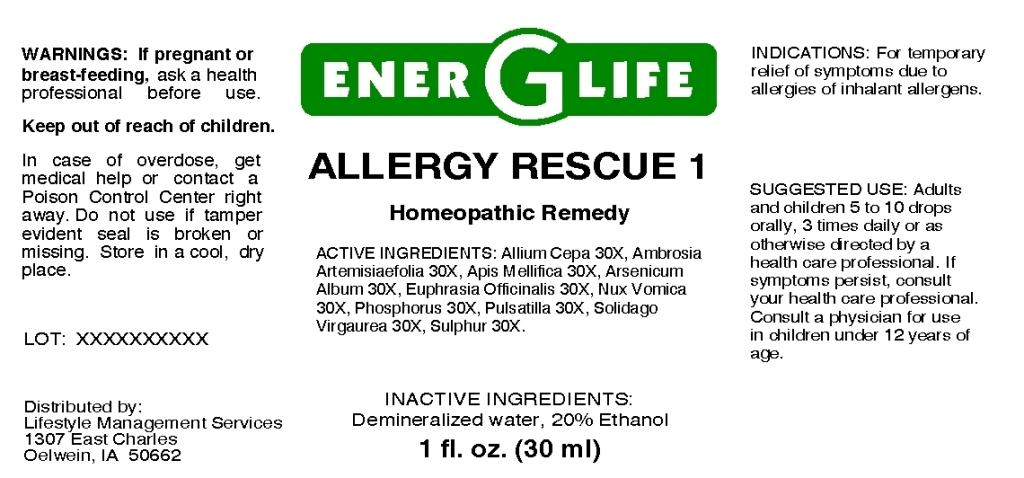 DRUG LABEL: Allergy Rescue 1
NDC: 57520-0651 | Form: LIQUID
Manufacturer: Apotheca Company
Category: homeopathic | Type: HUMAN OTC DRUG LABEL
Date: 20110407

ACTIVE INGREDIENTS: ONION 30 [hp_X]/1 mL; AMBROSIA ARTEMISIIFOLIA 30 [hp_X]/1 mL; APIS MELLIFERA 30 [hp_X]/1 mL; ARSENIC TRIOXIDE 30 [hp_X]/1 mL; EUPHRASIA STRICTA 30 [hp_X]/1 mL; STRYCHNOS NUX-VOMICA SEED 30 [hp_X]/1 mL; PHOSPHORUS 30 [hp_X]/1 mL; PULSATILLA VULGARIS 30 [hp_X]/1 mL; SOLIDAGO VIRGAUREA FLOWERING TOP 30 [hp_X]/1 mL; SULFUR 30 [hp_X]/1 mL
INACTIVE INGREDIENTS: WATER; ALCOHOL

Allergy Rescue 1

ACTIVE INGREDIENT

ACTIVE INGREDIENTS: Allium cepa 30X, Ambrosia artemisiaefolia 30X, Apis mellifica 30X, Euphrasia officinalis 30X, Nux vomica 30X, Phosphorus 30X, Pulsatilla 30X, Solidago virgaurea 30X, Sulphur 30X.

PURPOSE

INDICATIONS: For temporary relief of symptoms due to allergies of inhalant allergens.

WARNINGS

WARNINGS: If pregnant or breast-feeding, ask a health professional before use.

Keep out of reach of children. In case of overdose, get medical help or contact a Poison Control Center right away.

Do not use if tamper evident seal is broken or missing. Store in a cool, dry place.

DOSAGE AND ADMINISTRATION

SUGGESTED USE: Adults and children 5 to 10 drops orally, 3 times daily or as otherwise directed by a health care professional. If symptoms persist, consult your health care professional. Consult a physician for use in children under 12 years of age.

INACTIVE INGREDIENTS: Demineralized water, 20% Ethanol.

KEEP OUT OF REACH OF CHILDREN. In case of overdose, get medical help or contact a Poison Control Center right away.

INDICATIONS AND USAGE

INDICATIONS: For temporary relief of symptoms due to allergies of inhalant allergens.

QUESTIONS

Distributed by:

Lifestyle Management Services

1307 East Charles

Oelwein, IA 50662

PACKAGE LABEL

ENER G LIFE

ALLERGY RESCUE 1

Homeopathic Remedy

1 fl. oz. (30 ml)